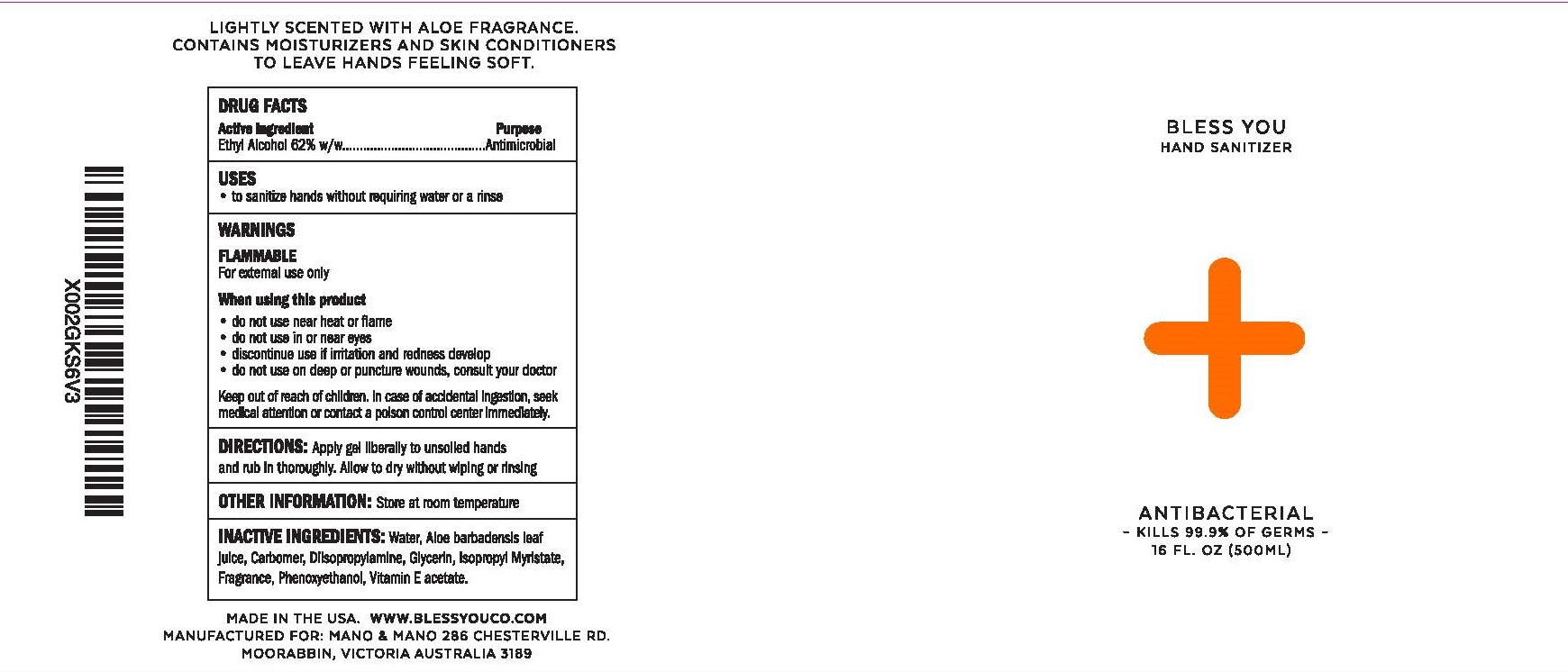 DRUG LABEL: Bless You
NDC: 73708-919 | Form: GEL
Manufacturer: CarrollClean LLC
Category: otc | Type: HUMAN OTC DRUG LABEL
Date: 20200825

ACTIVE INGREDIENTS: ALCOHOL 62 mL/100 mL
INACTIVE INGREDIENTS: ALOE VERA LEAF 0.8843 mL/100 mL; GLYCERIN 0.1431 mL/100 mL; .ALPHA.-TOCOPHEROL ACETATE 0.0093 mL/100 mL; WATER 36.0815 mL/100 mL; ISOPROPYL MYRISTATE 0.1051 mL/100 mL; PHENOXYETHANOL 0.0404 mL/100 mL; DIISOPROPYLAMINE 0.2724 mL/100 mL; CARBOMER INTERPOLYMER TYPE A (55000 CPS) 0.3906 mL/100 mL

Bless You

Active Ingredients

Ethyl Alcohol 62%...............Antimicrobial

Uses

*To sanitize hands without requiring water or a rinse

DIRECTIONS

Apply gel liberally to unsoiled hands

and rub in thoroughly. Allow to dry without wiping or rinsing.

OTHER INFORMATION

Store at room temperature.

INACTIVE INGREDIENTS

Water, Aloe barbadensis leaf juice, Carbomer, Diisopropylamine, Glycerin, Isopropyl Myristate, Fragrance, Phenoxyethanol, Vitamin E acetate.

Keep out of reach of children.

When Using this product

- do not use near heat or flame
- do not use in or near eyes
- discontinue use if irritation and redness develop
- do not use on deep or puncture wounds, consult your doctor